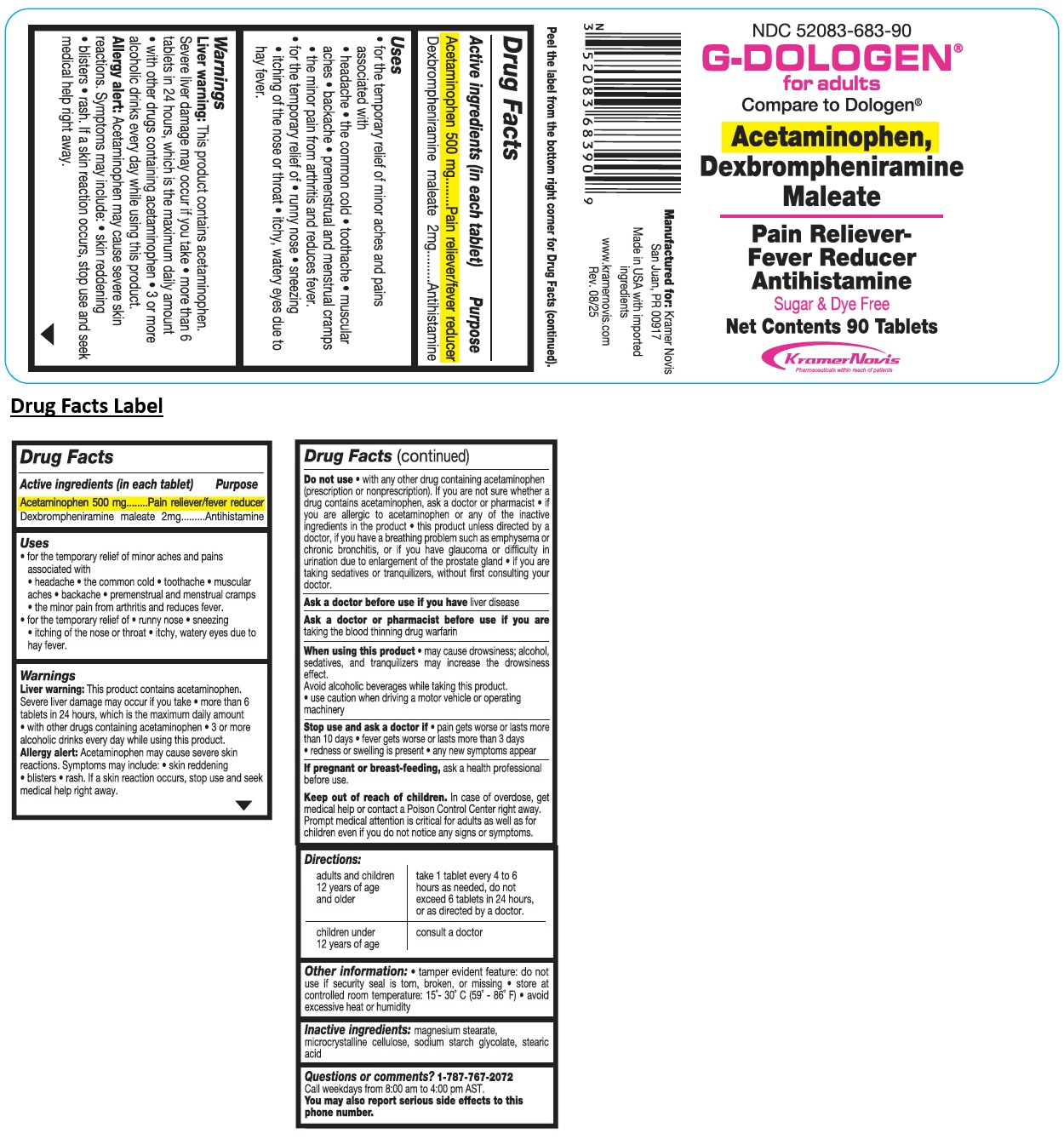 DRUG LABEL: G-DOLOGEN
NDC: 52083-683 | Form: TABLET
Manufacturer: Kramer Novis
Category: otc | Type: HUMAN OTC DRUG LABEL
Date: 20251205

ACTIVE INGREDIENTS: ACETAMINOPHEN 500 mg/1 1; DEXBROMPHENIRAMINE MALEATE 2 mg/1 1
INACTIVE INGREDIENTS: MAGNESIUM STEARATE; MICROCRYSTALLINE CELLULOSE; SODIUM STARCH GLYCOLATE TYPE A; STEARIC ACID

G-DOLOGEN® for adults

Active ingredients (in each tablet)

Acetaminophen 500 mg
Dexbrompheniramine maleate 2mg

Purpose

Pain reliever/fever reducer
Antihistamine

Uses

• for the temporary relief of minor aches and pains associated with
• headache • the common cold • toothache • muscular aches • backache • premenstrual and menstrual cramps • the minor pain from arthritis and reduces fever.
• for the temporary relief of • runny nose • sneezing • itching of the nose or throat • itchy, watery eyes due to hay fever.

Warnings

Liver warning: This product contains acetaminophen. Severe liver damage may occur if you take • more than 6 tablets in 24 hours, which is the maximum daily amount • with other drugs containing acetaminophen • 3 or more alcoholic drinks every day while using this product.
Allergy alert: Acetaminophen may cause severe skin reactions. Symptoms may include • skin reddening • blisters • rash. If a skin reaction occurs, stop use and seek medical help right away.

Do not use • with any other drug containing acetaminophen (prescription or nonprescription). If you are not sure whether a drug contains acetaminophen, ask a doctor or pharmacist • if you are allergic to acetaminophen or any of the inactive ingredients in the product • this product unless directed by a doctor, if you have a breathing problem such as emphysema or chronic bronchitis, or if you have glaucoma or difficulty in urination due to enlargement of the prostrate gland • if you are taking sedatives or tranquilizers, without first consulting your doctor.

Ask a doctor before use if you have liver disease

Ask a doctor or pharmacist before use if you are taking the blood thinning drug warfarin

When using this product • may cause drowsiness; alcohol, sedatives, and tranquilizers may increase the drowsiness effect.
Avoid alcoholic beverages while taking this product.
• use caution when driving a motor vehicle or operating machinery

Stop use and ask a doctor if • pain gets worse or lasts more than 10 days • fever gets worse or lasts more than 3 days • redness or swelling is present • any new symptoms appear

If pregnant or breast-feeding, ask a health professional before use.

Keep out of reach of children. In case of overdose, get medical help or contact a Poison Control Center right away. Prompt medical attention is critical for adults as well as for children even if you do not notice any signs or symptoms.

Directions:

adults and children 12 years of age and older | take 1 tablet every 4 to 6 hours as needed, do not exceed 6 tablets in 24 hours, or as directed by a doctor.
children under 12 years of age | consult a doctor

Other information:

• tamper evident feature: do not use if security seal is torn, broken, or missing • store at controlled room temperature: 15°- 30°C (59° - 86°F) • avoid excessive heat or humidity

Inactive ingredients:

magnesium stearate, microcrystalline cellulose, sodium starch glycolate, stearic acid

Questions or comments?

1-787-767-2072
Call weekdays from 8:00 am to 4.00 pm AST.
You may also report serious side effects to this phone number.

Compare to Dologen®

Sugar & Dye Free

Manufactured for: Kramer Novis
San Juan, PR 00917

Made in USA with imported ingredients

www.kramernovis.com

Peel the label from the bottom right corner for Drug Facts (continued).